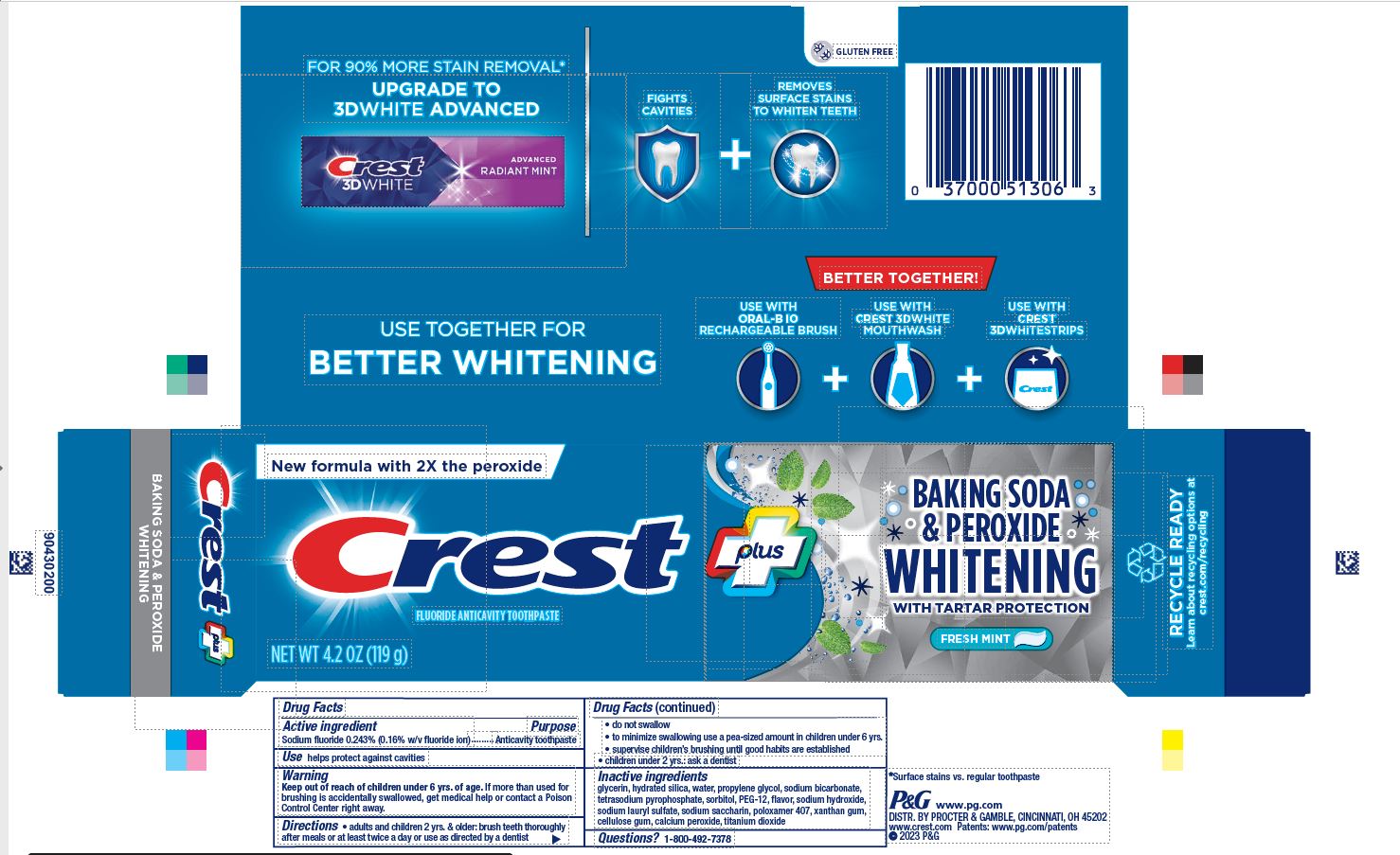 DRUG LABEL: Crest Plus Baking Soda and Peroxide
NDC: 69423-814 | Form: PASTE, DENTIFRICE
Manufacturer: The Procter & Gamble Manufacturing Company
Category: otc | Type: HUMAN OTC DRUG LABEL
Date: 20250225

ACTIVE INGREDIENTS: SODIUM FLUORIDE 1.6 mg/1 g
INACTIVE INGREDIENTS: HYDRATED SILICA; WATER; PROPYLENE GLYCOL; SODIUM BICARBONATE; SODIUM PYROPHOSPHATE; SORBITOL; POLYETHYLENE GLYCOL 600; GLYCERIN; SODIUM HYDROXIDE; SODIUM LAURYL SULFATE; SACCHARIN SODIUM; POLOXAMER 407; XANTHAN GUM; CARBOXYMETHYLCELLULOSE SODIUM; CALCIUM PEROXIDE; TITANIUM DIOXIDE

Crest®Baking Soda & Peroxide
Whitening with Tartar Protection

Drug Facts

Active ingredient

Sodium fluoride 0.243% (0.16% w/v fluoride ion)

Purpose

Anticavity toothpaste

Use

helps protect against cavities

Warning

Keep out of reach of children under 6 yrs. of age.If more than used for brushing is accidentally swallowed, get medical help or contact a Poison Control Center right away.

Directions

- adults and children 2 yrs. & older: brush teeth thoroughly after meals or at least twice a day or use as directed by a dentist
  - do not swallow
  - to minimize swallowing use a pea-sized amount in children under 6
  - supervise children's brushing until good habits are established
- children under 2 yrs.: ask a dentist

Inactive ingredients

glycerin, hydrated silica, water, propylene glycol, sodium bicarbonate, tetrasodium pyrophosphate, sorbitol, PEG-12, flavor, sodium hydroxide, sodium lauryl sulfate, sodium saccharin, poloxamer 407, xanthan gum, cellulose gum, calcium peroxide, titanium dioxide

Questions?

1-800-492-7378

Dist. by Procter & Gamble, Cincinnati, OH 45202

PRINCIPAL DISPLAY PANEL - 119 g Tube Carton

New Formula with 2X Peroxide

Crest Plus

Baking Soda & Peroxide

Whitening

With Tartar Protection

Fresh Mint

Net Wt 4.2 OZ (119g)